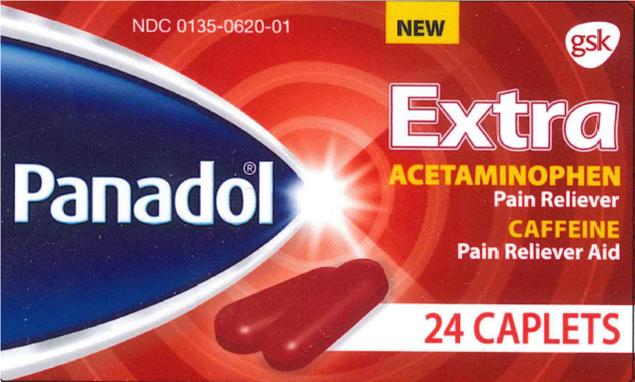 DRUG LABEL: PANADOL

NDC: 0135-0620 | Form: TABLET, FILM COATED
Manufacturer: Haleon US Holdings LLC
Category: otc | Type: HUMAN OTC DRUG LABEL
Date: 20240206

ACTIVE INGREDIENTS: ACETAMINOPHEN 500 mg/1 1; CAFFEINE 65 mg/1 1
INACTIVE INGREDIENTS: BENZOIC ACID; D&C RED NO. 27; ALUMINUM OXIDE; FD&C BLUE NO. 2; FD&C YELLOW NO. 6; MAGNESIUM STEARATE; MICROCRYSTALLINE CELLULOSE; POLYETHYLENE GLYCOL, UNSPECIFIED; POLYVINYL ALCOHOL, UNSPECIFIED; POVIDONE, UNSPECIFIED; STARCH, CORN; TITANIUM DIOXIDE; STEARIC ACID; TALC

Drug Facts

Active ingredient (in each caplet)

Acetaminophen 500 mg

Caffeine 65 mg

Purposes

Pain reliever

Pain reliever aid

Uses

- temporarily relieves minor aches and pains due to:
  - headache
  - muscular aches

Warnings

Liver warning:This product contains acetaminophen. Severe liver damage may occur if you take

- more than 8 caplets in 24 hours, which is the maximum daily amount
- with other drugs containing acetaminophen
- 3 or more alcoholic drinks every day while using this product

Allergy alert:acetaminophen may cause severe skin reactions. Symptoms may include:

- skin reddening
- blisters
- rash

If a skin reaction occurs, stop use and seek medical help right away.

Caffeine warning:The recommended dose of this product contains about as much caffeine as a cup of coffee. Limit the use of caffeine-containing medications, foods, or beverages while taking this product because too much caffeine may cause nervousness, irritability, sleeplessness, and, occasionally, rapid heartbeat.

Do not use

- with any other drug containing acetaminophen (prescription or nonprescription). If you are not sure whether a drug contains acetaminophen, ask a doctor or pharmacist.
- if you are allergic to acetaminophen, caffeine or any of the other ingredients in this product

Ask a doctor before use if you have

liver disease

Ask a doctor or pharmacist before use if you are

taking the blood thinning drug warfarin

Stop use and ask a doctor if

- pain gets worse or lasts more than 10 days
- fever gets worse or lasts more than 3 days
- redness or swelling is present
- any new symptoms occur

These could be signs of a serious condition.

If pregnant or breast-feeding,

ask a health professional before use.

Overdose warning:

Taking more than the recommended dose can cause serious health problems. In case of overdose, get medical help or contact a Poison Control Center right away. Quick medical attention is critical for adults as well as for children even if you do not notice any signs or symptoms.

Directions

- do not use more than directed(see overdose warming)
- adults and children 12 years of age and over: take 2 caplets every 6 hours, while symptoms persist or as directed by a doctor
- do not take more than 8 caplets in 24 hours, unless directed by a doctor
- children under 12 years: ask a doctor

Other information

- store at 20°-25°C (68°-77°F)
- close cap tightly after use

Inactive ingredients

benzoic acid, D&C red #27 aluminum lake, FD&C blue #2 aluminum lake, FD&C yellow #6 aluminum lake, magnesium stearate, microcrystalline cellulose, polyethylene glycol, polyvinyl alcohol, povidone, pregelatinized starch, stearic acid, talc titanium dioxide

Questions or comments?

1-800-455-7139

Principal Display Panel

NDC 0135-0620-01

Panadol®

EXTRA

ACETAMINOPHEN

Pain Reliever

CAFFEINE

Pain Reliever Aid

NEW

24 CAPLETS

TAMPER-EVIDENT BOTTLE

DO NOT USE IF INNER FOIL SEAL IMPRINTED WITH “SEALED for YOUR PROTECTION” IS BROKEN OR MISSING

READ AND KEEP CARTON FOR COMPLETE INFORMATION

Distributed by: GSKConsumer Healthcare, Warren, NJ 07059

©2016 GSK group of companies or its licensor. All rights reserved.

Trademarks are owned by or licensed to the GSK group of companies.

62000000011138